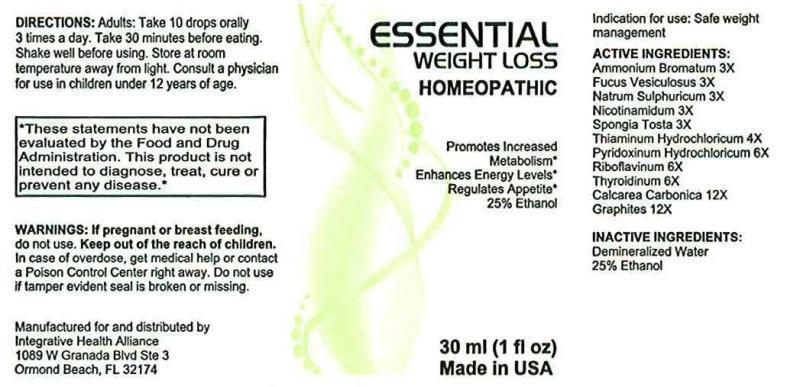 DRUG LABEL: ESSENTIAL WEIGHT LOSS
NDC: 69207-0001 | Form: LIQUID
Manufacturer: Integrative Health Alliance
Category: homeopathic | Type: HUMAN OTC DRUG LABEL
Date: 20191111

ACTIVE INGREDIENTS: AMMONIUM BROMIDE 3 [hp_X]/1 mL; FUCUS VESICULOSUS 3 [hp_X]/1 mL; SODIUM SULFATE 3 [hp_X]/1 mL; NIACINAMIDE 3 [hp_X]/1 mL; SPONGIA OFFICINALIS SKELETON, ROASTED 3 [hp_X]/1 mL; THIAMINE HYDROCHLORIDE 4 [hp_X]/1 mL; PYRIDOXINE HYDROCHLORIDE 6 [hp_X]/1 mL; RIBOFLAVIN 6 [hp_X]/1 mL; THYROID, BOVINE 6 [hp_X]/1 mL; OYSTER SHELL CALCIUM CARBONATE, CRUDE 12 [hp_X]/1 mL; GRAPHITE 12 [hp_X]/1 mL
INACTIVE INGREDIENTS: WATER; ALCOHOL

DRUG FACTS:

ACTIVE INGREDIENTS:

AMMONIUM BROMATUM 3X, FUCUS VESICULOSUS 3X, NATRUM SULPHURICUM 3X, NICOTINAMIDUM 3X, SPONGIA TOSTA 3X, THIAMINUM HYDROCHLORICUM 4X, PYRIDOXINUM HYDROCHLORICUM 6X, RIBOFLAVINUM 6X, THYROIDINUM (BOVINE) 6X, CALCAREA CARBONICA 12X, GRAPHITES 12X

INDICATION FOR USE:

Safe weight management

WARNINGS:

If pregnant or breast feeding, do not use.

Keep out of reach of children. In case of overdose, get medical help or contact a Poison Control Center right away.

Do not use if tamper evident seal is broken or missing.

Keep out of reach of children. In case of overdose, get medical help or contact a Poison Control Center right away.

DIRECTIONS:

Adults: Take 10 drops orally 3 times a day. Take 30 minutes before eating.

Shake well before using. Store at room temperature away from light.

Consult a physician for use in children under 12 years of age.

INDICATION FOR USE:

Safe weight management

INACTIVE INGREDIENTS:

Demineralized Water, Ethanol 25%

QUESTIONS:

Manufactured for and distributed by

Integrative Health Alliance

1089 Granada Blvd Ste 3

Ormond Beach, FL 32174

PACKAGE LABEL DISPLAY:

ESSENTIAL

WEIGHT LOSS

HOMEOPATHIC

Promotes Increased

Metabolism*

Enhances Energy Levels*

Regulates Appetite*

25%Ethanol

30 ml (1 fl oz)

Made in USA

*These statements have not been evaluated by the Food and Drug Administration.

This product is not intended to treat, cure or prevent any disease.*